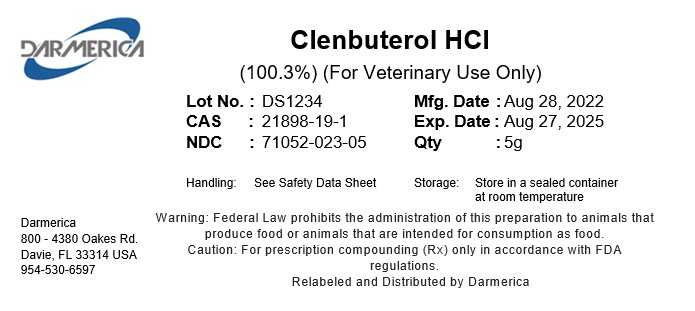 DRUG LABEL: Clenbuterol HCl
NDC: 71052-023 | Form: POWDER
Manufacturer: DARMERICA, LLC
Category: other | Type: BULK INGREDIENT - ANIMAL DRUG
Date: 20240108

ACTIVE INGREDIENTS: CLENBUTEROL HYDROCHLORIDE 100 g/100 g

Clenbuterol HCl